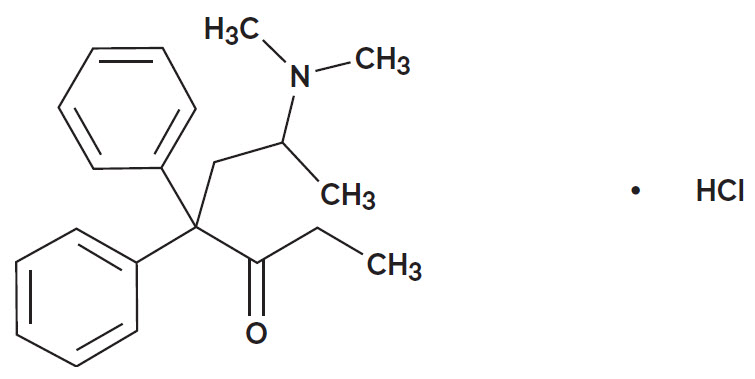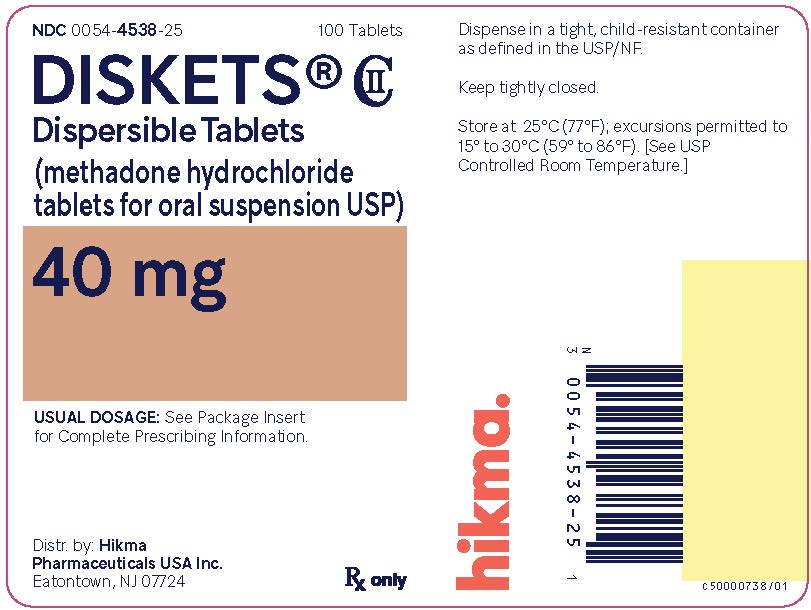 DRUG LABEL: DISKETS
NDC: 0054-4538 | Form: TABLET
Manufacturer: Hikma Pharmaceuticals USA Inc.
Category: prescription | Type: HUMAN PRESCRIPTION DRUG LABEL
Date: 20251201
DEA Schedule: CII

ACTIVE INGREDIENTS: METHADONE HYDROCHLORIDE 40 mg/1 1
INACTIVE INGREDIENTS: SILICON DIOXIDE; MAGNESIUM STEARATE; MICROCRYSTALLINE CELLULOSE 101; MONOBASIC POTASSIUM PHOSPHATE; STARCH, CORN; STEARIC ACID; FD&C YELLOW NO. 6

HIGHLIGHTS OF PRESCRIBING INFORMATION

These highlights do not include all the information needed to use DISKETS safely and effectively. See full prescribing information for DISKETS.
DISKETS (methadone hydrochloride) tablets, for oral suspension CII
Initial U.S. Approval: 1947

RECENT MAJOR CHANGES

Dosage and Administration (2.3, 2.7) 12/2025
Warnings and Precautions (5.1, 5.2, 5.13, 5.15) 12/2025

WARNING: LIFE-THREATENING RESPIRATORY DEPRESSION, LIFE-THREATENING QT PROLONGATION, ACCIDENTAL INGESTION, ABUSE POTENTIAL, INTERACTIONS WITH DRUGS AFFECTING CYTOCHROME P450 ISOENZYMES and TREATMENT FOR OPIOID ADDICTION

See full prescribing information for complete boxed warning.

- Fatal respiratory depression may occur, with highest risk at initiation and with dose increases. Instruct patients on proper administration of DISKETS Dispersible Tablets to reduce the risk. (5.1)
- Concomitant use with benzodiazepines or other central nervous system (CNS) depressants, including alcohol, may result in profound sedation, respiratory depression, and death. (5.2, 7)
- QT Interval prolongation and serious arrhythmia (torsades de pointes) have occurred with treatment with methadone. (5.3)
- Accidental ingestion of DISKETS Dispersible Tablets can result in fatal overdose of methadone, especially in children. (5.4)
- DISKETS Dispersible Tablets contain methadone, a Schedule II controlled substance and can be abused and criminally diverted. (5.5)
- Concomitant use with CYP3A4, 2B6, 2C19, 2C9 or 2D6 inhibitors or discontinuation of concomitantly used CYP3A4, 2B6, 2C19, or 2C9 inducers can result in a fatal overdose of methadone. (5.7, 7)
- Methadone products, when used for the treatment of opioid addiction in detoxification or maintenance programs, shall be dispensed only by certified opioid treatment programs as stipulated in 42 CFR 8.12. (2.1)

1 INDICATIONS AND USAGE

DISKETS Dispersible Tablets are an opioid agonist indicated for the:

- Detoxification treatment of opioid addiction (heroin or other morphine-like drugs). (1)
- Maintenance treatment of opioid addiction (heroin or other morphine-like drugs), in conjunction with appropriate social and medical services. (1)

Limitations of Use

- Methadone products used for the treatment of opioid addiction in detoxification or maintenance programs are subject to the conditions for distribution and use required under 21 CFR, Title 42, Sec 8. (1, 2.1)

2 DOSAGE AND ADMINISTRATION

- Strongly consider recommending or prescribing an opioid overdose reversal agent (e.g., naloxone, nalmefene) at the time DISKETS Dispersible Tablets is initiated or renewed because patients being treated with methadone may be at risk for opioid overdose during initiation or titration, or in the case of relapse to illicit use. (2.3)
- Initiation of Detoxification and Maintenance Treatment: A single dose of 20 to 30 mg may be sufficient to suppress withdrawal syndrome. (2.5)
- Maintenance Treatment: Clinical stability is most commonly achieved at doses between 80 to 120 mg/day. (2.6)
- Do not rapidly reduce or abruptly discontinue DISKETS Dispersible Tablets in a physically-dependent patient. (2.7, 5.15)

3 DOSAGE FORMS AND STRENGTHS

Tablets Intended for Dispersion in a Liquid Immediately Prior to Oral Administration: 40 mg. (3)

4 CONTRAINDICATIONS

- Significant respiratory depression (4)
- Acute or severe bronchial asthma (4)
- Known or suspected paralytic ileus (4)
- Known hypersensitivity to methadone (4)

5 WARNINGS AND PRECAUTIONS

- Neonatal Opioid Withdrawal Syndrome: Neonatal opioid withdrawal syndrome (NOWS) is an expected and treatable outcome of prolonged use of opioids during pregnancy. (5.6)
- Life-Threatening Respiratory Depression in Patients with Chronic Pulmonary Disease or in Elderly, Cachectic, or Debilitated Patients: Monitor closely, particularly during initiation and titration. (5.8)
- Serotonin Syndrome: Potentially life-threatening condition could result from concomitant serotonergic drug administration. Discontinue DISKETS if serotonin syndrome is suspected. (5.9)
- Adrenal Insufficiency: If diagnosed, treat with physiologic replacement of corticosteroids, and wean patient off of the opioid. (5.10)
- Severe Hypotension: Monitor during dose initiation and titration. (5.11)
- Risks of Use in Patients with Head Injury and Increased Intracranial Pressure: Monitor for sedation and respiratory depression. Avoid use of methadone in patients with impaired consciousness or coma susceptible to intracranial effects of CO2 retention. (5.12)

6 ADVERSE REACTIONS

Most Common Adverse Reactions Are: lightheadedness, dizziness, sedation, nausea, vomiting, and sweating. (6)

To report SUSPECTED ADVERSE REACTIONS, contact Hikma Pharmaceuticals USA Inc. at 1-800-962-8364 or FDA at 1-800-FDA-1088 or www.fda.gov/medwatch.

7 DRUG INTERACTIONS

- Potentially Arrhythmogenic Agents: Monitor patients closely for cardiac conduction changes. (7)
- Interactions with CNS Depressants: Consider dose reduction of one or both drugs because of additive effects. (7)
- Mixed Agonist/Antagonist and Partial Agonist Opioids: Avoid concomitant use with DISKETS because it may precipitate withdrawal symptoms. (5.15, 7)

8 USE IN SPECIFIC POPULATIONS

- Lactation: Monitor breastfed infants for increased drowsiness and breathing difficulties. (8.2)

FULL PRESCRIBING INFORMATION

WARNING: LIFE-THREATENING RESPIRATORY DEPRESSION, LIFE-THREATENING QT PROLONGATION, ACCIDENTAL INGESTION, ABUSE POTENTIAL, INTERACTIONS WITH DRUGS AFFECTING CYTOCHROME P450 ISOENZYMES and TREATMENT FOR OPIOID ADDICTION

Life-Threatening Respiratory Depression

Respiratory depression, including fatal cases, have been reported during initiation and conversion of patients to methadone, and even when the drug has been used as recommended and not misused or abused [see Warnings and Precautions (5.1)]. Proper dosing and titration are essential and DISKETS Dispersible Tablets should only be prescribed by healthcare professionals who are knowledgeable in the use of methadone for detoxification and maintenance treatment of opioid addiction. Monitor for respiratory depression, especially during initiation of DISKETS Dispersible Tablets or following a dose increase. The peak respiratory depressant effect of methadone occurs later, and persists longer than the peak pharmacologic effect, especially during the initial dosing period.

Managing Risks From Concomitant Use With Benzodiazepines or Other CNS Depressants

Concomitant use with benzodiazepines or other central nervous system (CNS) depressants,

including alcohol, is a risk factor for respiratory depression and death [see Warnings and Precautions (5.2), Drug Interactions (7)].

- Reserve concomitant prescribing of benzodiazepines or other CNS depressants in patients in methadone treatment to those for whom alternatives to benzodiazepines or other CNS depressants are inadequate.
- Follow patients for signs and symptoms of respiratory depression and sedation. If the patient is visibly sedated, evaluate the cause of sedation and consider delaying or omitting daily methadone dosing.

Life-Threatening QT Prolongation

QT interval prolongation and serious arrhythmia (torsades de pointes) have occurred during treatment with methadone [see Warnings and Precautions (5.3)]. Most cases involve patients being treated for pain with large, multiple daily doses of methadone, although cases have been reported in patients receiving doses commonly used for maintenance treatment of opioid addiction. Closely monitor patients with risk factors for development of prolonged QT interval, a history of cardiac conduction abnormalities, and those taking medications affecting cardiac conduction for changes in cardiac rhythm during initiation and titration of DISKETS Dispersible Tablets.

Accidental Ingestion

Accidental ingestion of DISKETS Dispersible Tablets, especially by children, can result in fatal overdose of methadone [see Warnings and Precautions (5.4)].

Misuse, Abuse, and Diversion of Opioids

DISKETS Dispersible Tablets contain methadone, an opioid agonist and Schedule II controlled substance with an abuse liability similar to other opioid agonists, legal or illicit [see Warnings and Precautions (5.5)].

Interactions with Drugs Affecting Cytochrome P450 Isoenzymes

The concomitant use of DISKETS with all cytochrome P450 3A4, 2B6, 2C19, 2C9 or 2D6 inhibitors may result in an increase in methadone plasma concentrations, which could cause potentially fatal respiratory depression. In addition, discontinuation of concomitantly used cytochrome P450 3A4, 2B6, 2C19, or 2C9 inducers may also result in an increase in methadone plasma concentration. Follow patients closely for respiratory depression and sedation, and consider dosage reduction with any changes of concomitant medications that can result in an increase in methadone levels [see Warnings and Precautions (5.7), Drug Interactions (7)].

Conditions For Distribution And Use Of Methadone Products For The Treatment of Opioid Addiction

For detoxification and maintenance of opioid dependence, methadone should be administered in accordance with the treatment standards cited in 42 CFR Section 8, including limitations on unsupervised administration [see Dosage and Administration (2.1)].

1 INDICATIONS AND USAGE

DISKETS Dispersible Tablets contain methadone, an opioid agonist indicated for the:

- Detoxification treatment of opioid addiction (heroin or other morphine-like drugs).
- Maintenance treatment of opioid addiction (heroin or other morphine-like drugs), in conjunction with appropriate social and medical services.

Limitations of Use

Methadone products used for the treatment of opioid addiction in detoxification or maintenance programs are subject to the conditions for distribution and use required under 42 CFR 8.12 [see Dosage and Administration (2.1)].

2 DOSAGE AND ADMINISTRATION

2.1 Conditions for Distribution and Use of Methadone Products for the Treatment of Opioid Addiction

Code of Federal Regulations, Title 42, Sec 8: Methadone products when used for the treatment of opioid addiction in detoxification or maintenance programs, shall be dispensed only by opioid treatment programs (and agencies, practitioners or institutions by formal agreement with the program sponsor) certified by the Substance Abuse and Mental Health Services Administration and approved by the designated state authority. Certified treatment programs shall dispense and use methadone in oral form only and according to the treatment requirements stipulated in the Federal Opioid Treatment Standards (42 CFR 8.12). See below for important regulatory exceptions to the general requirement for certification to provide opioid agonist treatment.

Failure to abide by the requirements in these regulations may result in criminal prosecution, seizure of the drug supply, revocation of the program approval, and injunction precluding operation of the program.

Regulatory Exceptions to the General Requirement for Certification to Provide Opioid Agonist Treatment:

- During inpatient care, when the patient was admitted for any condition other than concurrent opioid addiction (pursuant to 21CFR 1306.07(c)), to facilitate the treatment of the primary admitting diagnosis.
- During an emergency period of no longer than 3 days while definitive care for the addiction is being sought in an appropriately licensed facility (pursuant to 21 CFR 1306.07(b)).

2.2 Important Dosage and Administration Information

DISKETS Dispersible Tablets are for oral administration only. The preparation must not be injected. Methadone should be kept out of reach of children to prevent accidental ingestion.

Consider the following important factors that differentiate methadone from other opioids:

- The peak respiratory depressant effect of methadone occurs later and persists longer than its peak pharmacologic effect.
- A high degree of opioid tolerance does not eliminate the possibility of methadone overdose, iatrogenic or otherwise. Deaths have been reported during conversion to methadone from chronic, high-dose treatment with other opioid agonists and during initiation of methadone treatment of addiction in subjects previously abusing high doses of other opioid agonists.
- There is high interpatient variability in absorption, metabolism, and relative analgesic potency. Population-based conversion ratios between methadone and other opioids are not accurate when applied to individuals.
- With repeated dosing, methadone is retained in the liver and then slowly released, prolonging the duration of potential toxicity.
- Steady-state plasma concentrations are not attained until 3 to 5 days after initiation of dosing.

DISKETS have a narrow therapeutic index, especially when combined with other drugs.

2.3 Patient Access to an Opioid Overdose Reversal Agent for the Emergency Treatment of Opioid Overdose

Inform patients and caregivers about opioid overdose reversal agents (e.g., naloxone, nalmefene) and discuss the importance of having access to an opioid overdose reversal agent. Because patients being treated with methadone may be at risk for opioid overdose during initiation or titration, or in the case of relapse to illicit use, strongly consider recommending or prescribing an overdose reversal agent for the emergency treatment of opioid overdose, both when initiating and renewing treatment with DISKETS Dispersible Tablets. Also consider recommending or prescribing such an agent if the patient has household members (including children) or other close contacts at risk for accidental ingestion or opioid overdose [see Warnings and Precautions (5.1)].

Discuss the options for obtaining an opioid overdose reversal agent (e.g., prescription, over-the-counter, or as part of a community-based program) [see Warnings and Precautions (5.1)].

There are important differences among the opioid overdose reversal agents, such as route of administration, product strength, approved patient age range, and pharmacokinetics. Be familiar with these differences, as outlined in the approved labeling for those products, prior to recommending or prescribing such an agent.

Advise patients and caregivers that opioid overdose reversal agents, such as naloxone or nalmefene, may also be administered for a known or suspected overdose with DISKETS Dispersible Tablets itself [see Overdosage (10)].

2.4 Dosing Instructions

DISKETS are intended for dispersion in a liquid immediately prior to oral administration of the prescribed dose. The tablets should not be chewed or swallowed before dispersing in liquid.

DISKETS are cross-scored, allowing for flexible dosage adjustment. Each cross-scored tablet may be broken or cut in half to yield two 20-mg doses, or in quarters to yield four 10-mg doses.

Prior to administration, the desired dose of DISKETS should be dispersed in approximately 120 mL (4 ounces) of water, orange juice, or other acidic fruit beverage prior to taking. Methadone hydrochloride is very soluble in water, but there are some insoluble excipients that will not entirely dissolve. If residue remains in the cup after initial administration, a small amount of liquid should be added and the resulting mixture administered to the patient.

2.5 Induction/Initial Dosing for Detoxification and Maintenance Treatment of Opioid Addiction

For detoxification and maintenance of opioid dependence, methadone should be administered in accordance with the treatment standards cited in 42 CFR Section 8.12, including limitations on unsupervised administration.

Administer the initial methadone dose under supervision, when there are no signs of sedation or intoxication, and the patient shows symptoms of withdrawal. An initial single dose of 20 to 30 mg of methadone will often be sufficient to suppress withdrawal symptoms. The initial dose should not exceed 30 mg.

To make same-day dosing adjustments, have the patient wait 2 to 4 hours for further evaluation, when peak levels have been reached. Provide an additional 5 to 10 mg of methadone if withdrawal symptoms have not been suppressed or if symptoms reappear.

The total daily dose of methadone on the first day of treatment should not ordinarily exceed 40 mg. Adjust the dose over the first week of treatment based on control of withdrawal symptoms at the time of expected peak activity (i.e., 2 to 4 hours after dosing). When adjusting the dose, keep in mind that methadone will accumulate over the first several days of dosing; deaths have occurred in early treatment due to the cumulative effects. Because DISKETS can be administered only in 10 mg increments, DISKETS may not be the appropriate product for initial dosing in many patients. Instruct patients that the dose will “hold” for a longer period of time as tissue stores of methadone accumulate.

Use lower initial doses for patients whose tolerance is expected to be low at treatment entry. Any patient who has not taken opioids for more than 5 days may no longer be tolerant. Do not determine initial doses based on previous treatment episodes or dollars spent per day on illicit drug use. Also consider concurrent medications and the general condition and medical status of the patient when selecting the initial dose.

During the induction phase of methadone maintenance treatment, patients are being withdrawn from opioids and may have opioid withdrawal symptoms. Monitor patients for signs and symptoms of opioid withdrawal including: lacrimation, rhinorrhea, sneezing, yawning, excessive perspiration, goose-flesh, fever, chilling alternating with flushing, restlessness, irritability, weakness, anxiety, depression, dilated pupils, tremors, tachycardia, abdominal cramps, body aches, involuntary twitching and kicking movements, anorexia, nausea, vomiting, diarrhea, intestinal spasms, and weight loss and consider dose adjustment as indicated.

Short-term Detoxification:

For a brief course of stabilization followed by a period of medically supervised withdrawal, titrate the patient to a total daily dose of about 40 mg in divided doses to achieve an adequate stabilizing level. After 2 to 3 days of stabilization, gradually decrease the dose of methadone. Decrease the dose of methadone on a daily basis or at 2-day intervals, keeping the amount of methadone sufficient to keep withdrawal symptoms at a tolerable level. Hospitalized patients may tolerate a daily reduction of 20% of the total daily dose. Ambulatory patients may need a slower schedule. Because DISKETS can be administered only in 10 mg increments, DISKETS may not be the appropriate product for gradual dose reduction in many patients.

2.6 Titration and Maintenance Treatment of Opioid Dependence

Titrate patients in maintenance treatment to a dose that prevents opioid withdrawal symptoms for 24 hours, reduces drug hunger or craving, and blocks or attenuates the euphoric effects of self-administered opioids, ensuring that the patient is tolerant to the sedative effects of methadone. Most commonly, clinical stability is achieved at doses between 80 to 120 mg/day. During prolonged administration of methadone, monitor patients for persistent constipation and manage accordingly.

2.7 Medically Supervised Withdrawal after a Period of Maintenance Treatment for Opioid Addiction

There is considerable variability in the appropriate rate of methadone taper in patients choosing medically supervised withdrawal from methadone treatment. Dose reductions should generally be less than 10% of the established tolerance or maintenance dose, and 10 to 14-day intervals should elapse between dose reductions. Because DISKETS can be administered only in 10 mg increments, it may not be the appropriate product for gradual dose reduction in many patients. Apprise patients of the high risk of relapse to illicit drug use associated with discontinuation of methadone maintenance treatment. Do not rapidly reduce or abruptly discontinue DISKETS Dispersible tablets in patients who may be physically dependent on opioids [see Warnings and Precautions (5.15)].

2.8 Risk of Relapse in Patients on Methadone Maintenance Treatment of Opioid Addiction

Abrupt opioid discontinuation can lead to development of opioid withdrawal symptoms [see Drug Abuse and Dependence (9.3)]. Opioid withdrawal symptoms have been associated with an increased risk of relapse to illicit drug use in susceptible patients.

2.9 Considerations for Management of Acute Pain During Methadone Maintenance Treatment

Patients in methadone maintenance treatment for opioid dependence who experience physical trauma, postoperative pain or other acute pain cannot be expected to derive analgesia from their existing dose of methadone. Such patients should be administered analgesics, including opioids, in doses that would otherwise be indicated for non-methadone-treated patients with similar painful conditions. When opioids are required for management of acute pain in methadone maintenance patients, somewhat higher and/or more frequent doses will often be required than would be the case for non-tolerant patients due to the opioid tolerance induced by methadone.

2.10 Dosage Adjustment During Pregnancy

Methadone clearance may be increased during pregnancy. During pregnancy, a woman’s methadone dose may need to be increased or the dosing interval decreased [see Use in Specific Populations (8.1)].

3 DOSAGE FORMS AND STRENGTHS

40 mg dispersible tablet for oral administration following dispersion in a liquid: pillow-shaped, light-pinkish orange, cross-scored compressed dispersible tablet.

4 CONTRAINDICATIONS

DISKETS Dispersible Tablets are contraindicated in patients with:

- Significant respiratory depression [see Warnings and Precautions (5.1)].
- Acute or severe bronchial asthma in an unmonitored setting or in the absence of resuscitative equipment [see Warnings and Precautions (5.8)].
- Known or suspected gastrointestinal obstruction, including paralytic ileus [see Warnings and Precautions (5.13)].
- Hypersensitivity (e.g. anaphylaxis) to methadone or any other ingredient in DISKETS Dispersible Tablets [see Adverse Reactions (6)].

5 WARNINGS AND PRECAUTIONS

5.1 Life-Threatening Respiratory Depression

Serious, life-threatening, or fatal respiratory depression has been reported with the use of methadone, even when used as recommended. Respiratory depression, if not immediately recognized and treated, may lead to respiratory arrest and death. Respiratory depression from opioids is manifested by a reduced urge to breathe and a decreased rate of respiration, often associated with a “sighing” pattern of breathing (deep breaths separated by abnormally long pauses). Carbon dioxide (CO2) retention from opioid-induced respiratory depression can exacerbate the sedating effects of opioids. Management of respiratory depression may include close observation, supportive measures, and use of opioid overdose reversal agents, depending on the patient’s clinical status [see Overdosage (10)].

While serious, life-threatening, or fatal respiratory depression can occur at any time during the use of DISKETS, the risk is greatest during the initiation of therapy or following a dose increase. The peak respiratory depressant effect of methadone occurs later, and persists longer than the peak pharmacologic effect, especially during the initial dosing period. Monitor patients closely for respiratory depression, when initiating therapy with DISKETS and following dose increases.

Instruct patients against use by individuals other than the patient for whom methadone was prescribed and to keep methadone out of the reach of children, as such inappropriate use may result in fatal respiratory depression [see Patient Counseling Information (17)].

To reduce the risk of respiratory depression, proper dosing and titration of methadone are essential [see Dosage and Administration (2.5)]. Overestimating the methadone dosage when initiating treatment can result in fatal overdose with the first dose.

To further reduce the risk of respiratory depression, consider the following:

- Patients tolerant to other opioids may be incompletely tolerant to methadone. Incomplete cross-tolerance is of particular concern for patients tolerant to other mu-opioid agonists. Deaths have been reported during conversion from chronic, high-dose treatment with other opioid agonists. Follow induction directions closely to avoid inadvertent overdose [see Dosage and Administration (2.5)].
- Proper dosing and titration are essential and methadone should be overseen only by healthcare professionals who are knowledgeable in the pharmacokinetics and pharmacodynamics of methadone.

Educate patients and caregivers on how to recognize respiratory depression and emphasize the importance of calling 911 or getting emergency medical help right away in the event of a known or suspected overdose [see Patient Counseling Information (17)].

Opioids can cause sleep-related breathing disorders including central sleep apnea (CSA) and sleep-related hypoxemia. Opioid use increases the risk of CSA in a dose-dependent fashion. In patients who present with CSA, consider decreasing the opioid dosage using best practices for opioid taper [see Dosage and Administration (2)].

Patient Access to an Opioid Overdose Reversal Agent for the Emergency Treatment of Opioid Overdose

Inform patients and caregivers about opioid overdose reversal agents (e.g., naloxone, nalmefene) and discuss the importance of having access to an opioid overdose reversal agent. Because patients being treated with methadone may be at risk for opioid overdose during initiation or titration, or in the case of relapse to illicit use, strongly consider recommending or prescribing an opioid overdose reversal agent for the emergency treatment of an opioid overdose, both when initiating and renewing treatment with DISKETS Dispersible Tablets. Also consider recommending or prescribing such an agent if the patient has household members (including children) or other close contacts at risk for accidental ingestion or opioid overdose [see Dosage and Administration (2.3)].

Discuss the options for obtaining an opioid overdose reversal agent (e.g., prescription, over-the-counter, or as part of a community-based program).

There are important differences among the opioid overdose reversal agents, such as route of administration, product strength, approved patient age range, and pharmacokinetics. Be familiar with these differences, as outlined in the approved labeling for those products, prior to recommending or prescribing such an agent.

Advise patients and caregivers that an opioid overdose reversal agent, such as naloxone or nalmefene, may also be administered for a known or suspected overdose with DISKETS Dispersible Tablets itself [see Overdosage (10)].

Educate patients and caregivers on how to recognize respiratory depression, and how to use an opioid overdose reversal agent for the emergency treatment of opioid overdose. Emphasize the importance of calling 911 or getting emergency medical help, even if an opioid overdose reversal agent is administered.

5.2 Managing Risks from Concomitant Use of Benzodiazepines or Other CNS Depressants with Methadone

Concomitant use of methadone and benzodiazepines and/or other CNS depressants (e.g., alcohol, non-benzodiazepine sedative/hypnotics, anxiolytics, tranquilizers, muscle relaxants, general anesthetics, antipsychotics, gabapentinoids [gabapentin or pregabalin], and other opioids), increases the risk of adverse reactions, including overdose and death. Medication-assisted treatment of opioid use disorder, however, should not be categorically denied to patients taking these drugs. Prohibiting or creating barriers to treatment can pose an even greater risk of morbidity and mortality due to the opioid use disorder alone.

As a routine part of orientation to methadone treatment, educate patients about the risks of concomitant use of benzodiazepines, sedatives, opioid analgesics, or alcohol.

Develop strategies to manage use of prescribed or illicit benzodiazepines or other CNS depressants at admission to methadone treatment, or if it emerges as a concern during treatment. Adjustments to induction procedures and additional monitoring may be required. There is no evidence to support dose limitations or arbitrary caps of methadone as a strategy to address benzodiazepine use in methadone-treated patients. However, if a patient is sedated at the time of methadone dosing, ensure that a medically-trained health care provider evaluates the cause of sedation and delays or omits the methadone dose if appropriate.

Cessation of benzodiazepines or other CNS depressants is preferred in most cases of concomitant use. In some cases monitoring in a higher level of care for taper may be appropriate. In others, gradually tapering a patient off a prescribed benzodiazepine or other CNS depressant or decreasing to the lowest effective dose may be appropriate.

For patients in methadone treatment, benzodiazepines are not the treatment of choice for anxiety or insomnia. Before co-prescribing benzodiazepines, ensure that patients are appropriately diagnosed and consider alternative medications and non-pharmacologic treatments to address anxiety or insomnia. Ensure that other healthcare providers prescribing benzodiazepines or other CNS depressants are aware of the patient’s methadone treatment and coordinate care to minimize the risks associated with concomitant use.

If concomitant use is warranted, strongly consider recommending or prescribing an opioid overdose reversal agent, as is recommended for all patients on methadone treatment for opioid use disorder [see Warnings and Precautions (5.1)].

In addition, take measures to confirm that patients are taking the medications prescribed and not diverting or supplementing with illicit drugs. Toxicology screening should test for prescribed and illicit benzodiazepines [see Drug Interactions (7)].

5.3 Life-Threatening QT Prolongation

Cases of QT interval prolongation and serious arrhythmia (torsades de pointes) have been observed during treatment with methadone. These cases appear to be more commonly associated with, but not limited to, higher dose treatment (> 200 mg/day). Most cases involve patients being treated for pain with large, multiple daily doses of methadone, although cases have been reported in patients receiving doses commonly used for maintenance treatment of opioid addiction. In most patients on the lower doses typically used for maintenance, concomitant medications and/or clinical conditions such as hypokalemia were noted as contributing factors. However, the evidence strongly suggests that methadone possesses the potential for adverse cardiac conduction effects in some patients. The effects of methadone on the QT interval have been confirmed in in vivo laboratory studies, and methadone has been shown to inhibit cardiac potassium channels in in vitro studies.

Closely monitor patients with risk factors for development of prolonged QT interval (e.g., cardiac hypertrophy, concomitant diuretic use, hypokalemia, hypomagnesemia), a history of cardiac conduction abnormalities, and those taking medications affecting cardiac conduction. QT prolongation has also been reported in patients with no prior cardiac history who have received high doses of methadone.

Evaluate patients developing QT prolongation while on DISKETS Dispersible Tablets treatment for the presence of modifiable risk factors, such as concomitant medications with cardiac effects, drugs which might cause electrolyte abnormalities, and drugs which might act as inhibitors of methadone metabolism.

Only initiate therapy with DISKETS Dispersible Tablets in patients for whom the anticipated benefit outweighs the risk of QT prolongation and development of dysrhythmias that have been reported with high doses of methadone. The use of methadone in patients already known to have a prolonged QT interval has not been systematically studied.

5.4 Accidental Ingestion

Accidental ingestion of even one dose of DISKETS Dispersible Tablets, especially by children, can result in respiratory depression and death due to an overdose. Keep DISKETS Dispersible Tablets out of reach of children to prevent accidental ingestion [see Warnings and Precautions (5.1)].

5.5 Misuse, Abuse, and Diversion of Opioids

DISKETS Dispersible Tablets contain methadone, an opioid agonist and a Schedule II controlled substance. Methadone can be abused in a manner similar to other opioid agonists, legal or illicit. Opioid agonists are sought by drug abusers and people with addiction disorders and are subject to criminal diversion.

Contact local state professional licensing board or state-controlled substances authority for information on how to prevent and detect abuse or diversion of this product.

5.6 Neonatal Opioid Withdrawal Syndrome

Neonatal opioid withdrawal syndrome (NOWS) is an expected and treatable outcome of prolonged use of opioids during pregnancy, whether that use is medically-authorized or illicit. Unlike opioid withdrawal syndrome in adults, NOWS may be life-threatening if not recognized and treated in the neonate. Healthcare professionals should observe newborns for signs of NOWS and manage accordingly [see Use in Specific Populations (8.1)].

Advise pregnant women receiving opioid addiction treatment with DISKETS of the risk of neonatal opioid withdrawal syndrome and ensure that appropriate treatment will be available [see Use in Specific Populations (8.1)]. This risk must be balanced against the risk of untreated opioid addiction which often results in continued or relapsing illicit opioid use and is associated with poor pregnancy outcomes. Therefore, prescribers should discuss the importance and benefits of management of opioid addiction throughout pregnancy.

5.7 Risks of Concomitant Use of Cytochrome P450 3A4, 2B6, 2C19, 2C9, or 2D6 Inhibitors or Discontinuation of P450 3A4, 2B6, 2C19, or 2C9 Inducers

Concomitant use of DISKETS with CYP3A4, CYP2B6, CYP2C19, CYP2C9, or CYP2D6 inhibitors, may increase plasma concentrations of methadone, prolong opioid adverse reactions, and may cause potentially fatal respiratory depression, particularly when an inhibitor is added after a stable dose of DISKETS is achieved. Similarly, discontinuation of concomitant CYP3A4, CYP2B6, CYP2C19, or CYP2C9 inducers in DISKETS-treated patients may increase methadone plasma concentrations resulting in fatal respiratory depression. Consider dosage reduction of DISKETS when using concomitant CYP3A4, CYP2B6, CYP2C19, CYP2C9 or CYP2D6 inhibitors or discontinuing CYP3A4, CYP2B6, CYP2C19, or CYP2C9 inducers in methadone-treated patients, and follow patients closely at frequent intervals for signs and symptoms of respiratory depression and sedation [see Drug Interactions (7)].

Addition of CYP3A4, CYP2B6, CYP2C19, or CYP2C9 inducers or discontinuation of CYP3A4, CYP2B6, CYP2C19, CYP2C9, or CYP2D6 inhibitors in patients treated with DISKETS may decrease methadone plasma concentrations, reducing efficacy and may lead to opioid withdrawal symptoms in patients physically dependent on methadone. When using DISKETS with CYP3A4, CYP2B6, CYP2C19, or CYP2C9 inducers or discontinuing CYP3A4, CYP2B6, CYP2C19, CYP2C9, or CYP2D6 inhibitors, follow patients for signs or symptoms of opioid withdrawal and consider increasing the DISKETS dosage as needed [see Drug Interactions (7)].

5.8 Life-Threatening Respiratory Depression in Patients with Chronic Pulmonary Disease or in Elderly, Cachectic, or Debilitated Patients

The use of DISKETS in patients with acute or severe bronchial asthma in an unmonitored setting or in the absence of resuscitative equipment is contraindicated.

Patients with Chronic Pulmonary Disease:

DISKETS-treated patients with significant chronic obstructive pulmonary disease or cor pulmonale, and those with a substantially decreased respiratory reserve, hypoxia, hypercapnia, or pre-existing respiratory depression are at increased risk of decreased respiratory drive including apnea, even at recommended dosages of DISKETS [see Warnings and Precautions (5.1)].

Elderly, Cachectic, or Debilitated Patients:

Life-threatening respiratory depression is more likely to occur in elderly, cachectic, or debilitated patients because they may have altered pharmacokinetics or altered clearance compared to younger, healthier patients [see Warnings and Precautions (5.1)].

Monitor such patients closely, particularly when initiating and titrating DISKETS and when DISKETS is given concomitantly with other drugs that depress respiration [see Warnings and Precautions (5.2)].

5.9 Serotonin Syndrome with Concomitant Use of Serotonergic Drugs

Cases of serotonin syndrome, a potentially life-threatening condition, have been reported during concomitant use of DISKETS with serotonergic drugs. Serotonergic drugs include selective serotonin reuptake inhibitors (SSRIs), serotonin and norepinephrine reuptake inhibitors (SNRIs), tricyclic antidepressants (TCAs), triptans, 5-HT3 receptor antagonists, drugs that affect the serotonergic neurotransmitter system (e.g., mirtazapine, trazodone, tramadol), certain muscle relaxants (i.e., cyclobenzaprine, metaxalone), and drugs that impair metabolism of serotonin (including MAO inhibitors, both those intended to treat psychiatric disorders and also others, such as linezolid and intravenous methylene blue) [see Drug Interactions (7)]. This may occur within the recommended dosage range.

Serotonin syndrome symptoms may include mental status changes (e.g., agitation, hallucinations, coma), autonomic instability (e.g., tachycardia, labile blood pressure, hyperthermia), neuromuscular aberrations (e.g., hyperreflexia, incoordination, rigidity), and/or gastrointestinal symptoms (e.g., nausea, vomiting, diarrhea). The onset of symptoms generally occurs within several hours to a few days of concomitant use, but may occur later than that. Discontinue DISKETS if serotonin syndrome is suspected.

5.10 Adrenal Insufficiency

Cases of adrenal insufficiency have been reported with opioid use, more often following greater than one month of use. Presentation of adrenal insufficiency may include non-specific symptoms and signs including nausea, vomiting, anorexia, fatigue, weakness, dizziness, and low blood pressure. If adrenal insufficiency is suspected, confirm the diagnosis with diagnostic testing as soon as possible. If adrenal insufficiency is diagnosed, treat with physiologic replacement doses of corticosteroids. Wean the patient off of the opioid to allow adrenal function to recover and continue corticosteroid treatment until adrenal function recovers. Other opioids may be tried as some cases reported use of a different opioid without recurrence of adrenal insufficiency. The information available does not identify any particular opioids as being more likely to be associated with adrenal insufficiency.

5.11 Severe Hypotension

Methadone may cause severe hypotension including orthostatic hypotension and syncope in ambulatory patients. There is an increased risk in patients whose ability to maintain normal blood pressure is compromised by a reduced blood volume or concurrent administration of certain CNS depressant drugs (e.g. phenothiazines or general anesthetics) [see Drug Interactions (7)]. Monitor these patients for signs of hypotension after initiating or titrating the dosage of DISKETS Dispersible Tablets. In patients with circulatory shock, DISKETS may cause vasodilation that can further reduce cardiac output and blood pressure. Avoid the use of DISKETS in patients with circulatory shock.

5.12 Risks of Use in Patients with Increased Intracranial Pressure, Brain Tumors, Head Injury, or Impaired Consciousness

In patients who may be susceptible to the intracranial effects of CO2 retention (e.g., those with evidence of increased intracranial pressure or brain tumors), DISKETS may reduce respiratory drive, and the resultant CO2 retention can further increase intracranial pressure. Monitor such patients for signs of sedation and respiratory depression, particularly when initiating therapy with methadone.

Opioids may also obscure the clinical course in a patient with a head injury.

Avoid the use of methadone in patients with impaired consciousness or coma.

5.13 Risks of Gastrointestinal Complications

DISKETS Dispersible Tablets are contraindicated in patients with known or suspected gastrointestinal obstruction, including paralytic ileus.

The methadone in DISKETS may cause spasm of the sphincter of Oddi. Opioids may cause increases in the serum amylase. Monitor patients with biliary tract disease, including acute pancreatitis, for worsening symptoms.

Cases of opioid-induced esophageal dysfunction (OIED) have been reported in patients taking opioids. The risk of OIED may increase as the dose and/or duration of opioids increases. Regularly evaluate patients for signs and symptoms of OIED (e.g., dysphagia, regurgitation, non-cardiac chest pain) and, if necessary, adjust opioid therapy as clinically appropriate [see Clinical Pharmacology (12.2)].

5.14 Increased Risks of Seizure in Patients with Seizure Disorders

Methadone may increase frequency of seizures in patients with seizure disorders, and increase the risks of seizures occurring in other clinical settings associated with seizures. Monitor patients with a history of seizure disorders for worsened seizure control during DISKETS Dispersible Tablets therapy.

5.15 Withdrawal

Avoid the use of mixed agonist/antagonist (i.e., pentazocine, nalbuphine, and butorphanol) or partial agonist (e.g., buprenorphine) analgesics in patients who are receiving a full opioid agonist, including DISKETS Dispersible Tablets. In these patients, mixed agonists/antagonist and partial agonist analgesics may precipitate withdrawal symptoms [see Drug Interactions (7)].

When discontinuing DISKETS Dispersible Tablets, gradually taper the dosage [see Dosage and Administration (2.7, 2.8)]. Do not rapidly reduce or abruptly discontinue DISKETS Dispersible Tablets [see Drug Abuse and Dependence (9.3)].

5.16 Risks of Driving and Operating Machinery

DISKETS Dispersible Tablets may impair the mental or physical abilities needed to perform potentially hazardous activities such as driving a car or operating machinery. Warn patients not to drive or operate dangerous machinery unless they are tolerant to the effects of DISKETS Dispersible Tablets and know how they will react to the medication [see Patient Counseling Information (17)].

5.17 Hypoglycemia

Cases of methadone-associated hypoglycemia have been reported, some resulting in hospitalization. In many cases, patients had predisposing risk factors (e.g., diabetes). The relationship between methadone and hypoglycemia is not fully understood but may be dose dependent. If hypoglycemia is suspected, monitor blood glucose levels, and manage the patient as clinically appropriate.

5.18 Laboratory Test Interactions

False positive urine drug screens for methadone have been reported for several drugs including diphenhydramine, doxylamine, clomipramine, chlorpromazine, thioridazine, quetiapine, and verapamil.

6 ADVERSE REACTIONS

The following serious adverse reactions and/or conditions are described, or described in greater detail, in other sections:

- Respiratory Depression [see Warnings and Precautions (5.1)]
- Interactions with Benzodiazepines and other CNS Depressants [see Warnings and Precautions (5.2)]
- QT Prolongation [see Warnings and Precautions (5.3)]
- Serotonin Syndrome [see Warnings and Precautions (5.9)]
- Adrenal Insufficiency [see Warnings and Precautions (5.10)]
- Severe Hypotension [see Warnings and Precautions (5.11)]
- Gastrointestinal Adverse Reactions [see Warnings and Precautions (5.13)]
- Seizures [see Warnings and Precautions (5.14)]
- Withdrawal [see Warnings and Precautions (5.15)]
- Hypoglycemia [see Warnings and Precautions (5.17)]

The following adverse reactions have been identified during post-approval use of methadone. Because these reactions are reported voluntarily from a population of uncertain size, it is not always possible to reliably estimate their frequency or establish a causal relationship to drug exposure.

The major hazards of methadone are respiratory depression and, to a lesser degree, systemic hypotension. Respiratory arrest, shock, cardiac arrest, and death have occurred.

The most frequently observed adverse reactions included lightheadedness, dizziness, sedation, nausea, vomiting, and sweating. These effects seemed to be more prominent in ambulatory patients and in those who are not suffering severe pain.

Other adverse reactions include the following:

Body as a Whole: asthenia (weakness), edema, headache

Cardiovascular: arrhythmias, bigeminal rhythms, bradycardia, cardiomyopathy, ECG abnormalities, extrasystoles, flushing, heart failure, hypotension, palpitations, phlebitis, QT interval prolongation, syncope, T-wave inversion, tachycardia, torsade de pointes, ventricular fibrillation, ventricular tachycardia.

Central Nervous System: agitation, confusion, disorientation, dysphoria, euphoria, insomnia, hallucinations, seizures, visual disturbances, congenital oculomotor disorders (nystagmus, strabismus)

Endocrine: hypogonadism

Gastrointestinal: abdominal pain, anorexia, biliary tract spasm, constipation, dry mouth, glossitis

Hematologic: Reversible thrombocytopenia has been described in opioid addicts with chronic hepatitis.

Metabolic: hypokalemia, hypomagnesemia, weight gain

Musculoskeletal: decreased muscle mass and strength, osteoporosis and fractures

Renal: antidiuretic effect, urinary retention or hesitancy

Reproductive: amenorrhea, reduced libido and/or potency, reduced ejaculate volume, reduced seminal vesicle and prostate secretions, decreased sperm motility, abnormalities in sperm morphology

Respiratory: pulmonary edema, respiratory depression

Skin and Subcutaneous Tissue: pruritus, urticaria, other skin rashes, and rarely, hemorrhagic urticaria

Hypersensitivity: Anaphylaxis has been reported with ingredients contained in DISKETS Dispersible Tablets.

Serotonin Syndrome: Cases of serotonin syndrome, a potentially life-threatening condition, have been reported during concomitant use of opioids with serotonergic drugs.

Adrenal Insufficiency: Cases of adrenal insufficiency have been reported with opioid use, more often following greater than one month of use.

Anaphylaxis: Anaphylaxis has been reported with ingredients contained in DISKETS.

Androgen Deficiency: Cases of androgen deficiency have occurred with chronic use of opioids [see Clinical Pharmacology (12.2)].

Hypoglycemia: Cases of hypoglycemia have been reported in patients taking methadone [see Warnings and Precautions (5.17)].

Opioid-induced esophageal dysfunction (OIED): Cases of OIED have been reported in patients taking opioids and may occur more frequently in patients taking higher doses of opioids, and/or in patients taking opioids longer term [see Warnings and Precautions (5.13)].

7 DRUG INTERACTIONS

Table 1: Clinically Significant Drug Interactions with DISKETS Dispersible Tablets
Benzodiazepines and Other Central Nervous System (CNS) Depressants
Clinical Impact: | Due to additive pharmacologic effect, the concomitant use of benzodiazepines or other CNS depressants, including alcohol, increases the risk of respiratory depression, profound sedation, coma, and death.
Intervention: | Cessation of benzodiazepines or other CNS depressants is preferred in most cases of concomitant use. In some cases, monitoring in a higher level of care for taper may be appropriate. In others, gradually tapering a patient off of a prescribed benzodiazepine or other CNS depressant or decreasing to the lowest effective dose may be appropriate.; Before co-prescribing benzodiazepines for anxiety or insomnia, ensure that patients are appropriately diagnosed and consider alternative medications and non-pharmacologic treatments [see Warnings and Precautions (5.2)].; If concomitant use is warranted, strongly consider recommending or prescribing an opioid overdose reversal agent, as is recommended for all patients in treatment for opioid use disorder [see Warnings and Precautions (5.1)].
Examples: | Benzodiazepines and other sedatives/hypnotics, anxiolytics, tranquilizers, muscle relaxants, general anesthetics, antipsychotics, gabapentinoids (gabapentin or pregabalin), other opioids, alcohol.
Inhibitors of CYP3A4, CYP2B6, CYP2C19, CYP2C9, or CYP2D6
Clinical Impact: | Methadone undergoes hepatic N-demethylation by several cytochrome P450 (CYP) isoforms, including CYP3A4, CYP2B6, CYP2C19, CYP2C9, and CYP2D6. The concomitant use of DISKETS Dispersible Tablets and CYP3A4, CYP2B6, CYP2C19, CYP2C9, or CYP2D6 inhibitors can increase the plasma concentration of methadone, resulting in increased or prolonged opioid effects, and may result in a fatal overdose, particularly when an inhibitor is added after a stable dose of DISKETS Dispersible Tablets is achieved. These effects may be more pronounced with concomitant use of drugs that inhibit more than one of the CYP enzymes listed above.; After stopping a CYP3A4, CYP2B6, CYP2C19, CYP2C9, or CYP2D6 inhibitor, as the effects of the inhibitor decline, the methadone plasma concentration can decrease [see Clinical Pharmacology (12.3)], resulting in decreased opioid efficacy or withdrawal symptoms in patients physically dependent on methadone.
Intervention: | If concomitant use is necessary, consider dosage reduction of DISKETS Dispersible Tablets until stable drug effects are achieved. Monitor patients for respiratory depression and sedation at frequent intervals.; If a CYP3A4, CYP2B6, CYP2C19, CYP2C9, or CYP2D6 inhibitor is discontinued, follow patients for signs of opioid withdrawal and consider increasing the DISKETS Dispersible Tablets dosage until stable drug effects are achieved.
Examples: | Macrolide antibiotics (e.g., erythromycin), azole-antifungal agents (e.g. ketoconazole), protease inhibitors (e.g., ritonavir), fluconazole, fluvoxamine, some selective serotonin reuptake inhibitors (SSRIs) (e.g., sertraline, fluvoxamine).
Inducers of CYP3A4, CYP2B6, CYP2C19, or CYP2C9
Clinical Impact: | The concomitant use of DISKETS Dispersible Tablets and CYP3A4, CYP2B6, CYP2C19, or CYP2C9 inducers can decrease the plasma concentration of methadone [see Clinical Pharmacology (12.3)], resulting in decreased efficacy or onset of withdrawal symptoms in patients physically dependent on methadone. These effects could be more pronounced with concomitant use of drugs that can induce multiple CYP enzymes.; After stopping a CYP3A4, CYP2B6, CYP2C19, or CYP2C9 inducer, as the effects of the inducer decline, the methadone plasma concentration can increase [see Clinical Pharmacology (12.3)], which could increase or prolong both the therapeutic effects and adverse reactions, and may cause serious respiratory depression, sedation, or death.
Intervention: | If concomitant use is necessary, consider increasing the DISKETS Dispersible Tablets dosage until stable drug effects are achieved. Monitor for signs of opioid withdrawal. If a CYP3A4, CYP2B6, CYP2C19, or CYP2C9 inducer is discontinued, consider DISKETS Dispersible Tablets dosage reduction and monitor for signs of respiratory depression and sedation.
Examples: | Rifampin, carbamazepine, phenytoin, St. John’s Wort, phenobarbital.
Potentially Arrhythmogenic Agents
Clinical Impact: | Pharmacodynamic interactions may occur with concomitant use of methadone and potentially arrhythmogenic agents or drugs capable of inducing electrolyte disturbances (hypomagnesemia, hypokalemia).
Intervention: | Monitor patients closely for cardiac conduction changes.
Examples: | Drugs known to have potential to prolong QT interval: Class I and III antiarrhythmics, some neuroleptics and tricyclic antidepressants, and calcium channel blockers. Drugs capable of inducing electrolyte disturbances: Diuretics, laxatives, and, in rare cases, mineralocorticoid hormones.
Serotonergic Drugs
Clinical Impact: | The concomitant use of opioids with other drugs that affect the serotonergic neurotransmitter system has resulted in serotonin syndrome [see Warnings and Precautions (5.9)].
Intervention: | If concomitant use is warranted, carefully observe the patient, particularly during treatment initiation and dose adjustment. Discontinue DISKETS if serotonin syndrome is suspected.
Examples: | Selective serotonin reuptake inhibitors (SSRIs), serotonin and norepinephrine reuptake inhibitors (SNRIs), tricyclic antidepressants (TCAs), triptans, 5-HT3 receptor antagonists, drugs that effect the serotonin neurotransmitter system (e.g., mirtazapine, trazodone, tramadol), certain muscle relaxants (i.e., cyclobenzaprine, metaxalone), monoamine oxidase (MAO) inhibitors (those intended to treat psychiatric disorders and also others, such as linezolid and intravenous methylene blue).
Monoamine Oxidase Inhibitors (MAOIs)
Clinical Impact: | MAOI interactions with opioids may manifest as serotonin syndrome or opioid toxicity (e.g., respiratory depression, coma) [see Warnings and Precautions (5.1, 5.9)].
Intervention: | The use of DISKETS is not recommended for patients taking MAOIs or within 14 days of stopping such treatment.
Examples: | Phenelzine, tranylcypromine, linezolid.
Mixed Agonist/Antagonist and Partial Agonist Opioid Analgesics
Clinical Impact: | Patients maintained on methadone may experience withdrawal symptoms when given opioid antagonists, mixed agonist/antagonists, and partial agonists.
Intervention: | Avoid concomitant use.
Examples: | Butorphanol, nalbuphine, pentazocine, buprenorphine.
Muscle Relaxants
Clinical Impact: | Methadone may enhance the neuromuscular blocking action of skeletal muscle relaxants and produce an increased degree of respiratory depression.
Intervention: | Monitor patients receiving muscle relaxants and DISKETS Dispersible Tablets for signs of respiratory depression that may be greater than otherwise expected and decrease the dosage of the muscle relaxant as necessary. Due to the risk of respiratory depression with concomitant use of skeletal muscle relaxants and opioids, strongly consider recommending or prescribing an opioid overdose reversal agent, as is recommended for all patients in treatment for opioid use disorder [see Dosage and Administration (2.3), Warnings and Precautions (5.1, 5.2)].
Examples: | cyclobenzaprine, metaxalone
Diuretics
Clinical Impact: | Opioids can reduce the efficacy of diuretics by inducing the release of antidiuretic hormone.
Intervention: | Monitor patients for signs of diminished diuresis and/or effects on blood pressure and increase the dosage of the diuretic as needed.
Anticholinergic Drugs
Clinical Impact: | The concomitant use of anticholinergic drugs may increase risk of urinary retention and/or severe constipation, which may lead to paralytic ileus.
Intervention: | Monitor patients for signs of urinary retention or reduced gastric motility when DISKETS are used concomitantly with anticholinergic drugs.

Paradoxical Effects of Antiretroviral Agents on Methadone:

Concurrent use of certain protease inhibitors with CYP3A4 inhibitory activity, alone and in combination, such as abacavir, amprenavir, darunavir+ritonavir, efavirenz, nelfinavir, nevirapine, ritonavir, telaprevir, lopinavir+ritonavir, saquinavir+ritonavir, and tipranavir+ritonavir, has resulted in increased clearance or decreased plasma levels of methadone. This may result in reduced efficacy of DISKETS Dispersible Tablets and could precipitate a withdrawal syndrome. Monitor patients receiving DISKETS Dispersible Tablets and any of these anti-retroviral therapies closely for evidence of withdrawal effects and adjust the DISKETS Dispersible Tablets dose accordingly.

Effects of Methadone on Antiretroviral Agents:

Didanosine and Stavudine: Experimental evidence demonstrated that methadone decreased the area under the concentration-time curve (AUC) and peak levels for didanosine and stavudine, with a more significant decrease for didanosine. Methadone disposition was not substantially altered.

Zidovudine: Experimental evidence demonstrated that methadone increased the AUC of zidovudine, which could result in toxic effects.

Effects of Methadone on Antidepressants:

Desipramine: Blood levels of desipramine have increased with concurrent methadone administration.

8 USE IN SPECIFIC POPULATIONS

8.1 Pregnancy

Risk Summary

The majority of available data from clinical trials, observational studies, case series, and case reports on methadone use in pregnancy do not indicate an increased risk of major malformations specifically due to methadone.

Pregnant women involved in methadone maintenance programs have been reported to have improved prenatal care leading to reduced incidence of obstetric and fetal complications and neonatal morbidity and mortality when compared to women using illicit drugs. Several factors, including maternal use of illicit drugs, nutrition, infection and psychosocial circumstances, complicate the interpretation of investigations of the children of women who take methadone during pregnancy. Information is limited regarding dose and duration of methadone use during pregnancy, and most maternal exposure in these studies appears to occur after the first trimester of pregnancy (see Data).

Neonatal opioid withdrawal syndrome (NOWS) is an expected and treatable outcome of prolonged use of opioids during pregnancy [see Warnings and Precautions (5.6)].

In published animal reproduction studies, methadone administered subcutaneously during the early gestational period produced neural tube defects (i.e., exencephaly and cranioschisis) in the hamster at doses 2 times the human daily oral dose of 120 mg/day on a mg/m^2 basis (HDD) and in mice at doses equivalent to the HDD. Administration of methadone to pregnant animals during organogenesis and through lactation resulted decreased litter size, increased pup mortality, decreased pup body weights, developmental delays, and long-term neurochemical changes in the brain of offspring which correlate with altered behavioral responses that persist through adulthood at exposures comparable to and less than the HDD. Administration of methadone to male rodents prior to mating with untreated females resulted in increased neonatal mortality and significant differences in behavioral tests in the offspring at exposures comparable to and less than the HDD (see Data). Based on animal data, advise pregnant women of the potential risk to a fetus.

The estimated background risk of major birth defects and miscarriage for the indicated population is unknown. All pregnancies have a background risk of birth defect, loss, or other adverse outcomes. In the U.S. general population, the estimated background risk of major birth defects and miscarriage in clinically recognized pregnancies is 2% to 4% and 15% to 20%, respectively.

Clinical Considerations

Disease-associated Maternal and Embryo-fetal Risk: Untreated opioid addiction in pregnancy is associated with adverse obstetrical outcomes such as low birth weight, preterm birth, and fetal death. In addition, untreated opioid addiction often results in continued or relapsing illicit opioid use.

Dosage Adjustment During Pregnancy: Dosage adjustment using higher doses or administering the daily dose in divided doses may be necessary in pregnant women treated with DISKETS. Pregnant women appear to have significantly lower trough plasma methadone concentrations, increased plasma methadone clearance, and shorter methadone half-life than after delivery [see Dosage and Administration (2.10) and Clinical Pharmacology (12.3)]. Withdrawal signs and symptoms should be closely monitored and the dose adjusted as necessary.

Fetal/Neonatal Adverse Reactions: Neonatal opioid withdrawal syndrome may occur in newborn infants of mothers who are receiving treatment with DISKETS. Neonatal opioid withdrawal syndrome presents as irritability, hyperactivity and abnormal sleep pattern, high pitched cry, tremor, vomiting, diarrhea, and/or failure to gain weight. Signs of neonatal withdrawal usually occur in the first days after birth. The duration and severity of neonatal opioid withdrawal syndrome may vary. Observe newborns for signs of neonatal opioid withdrawal syndrome and manage accordingly [see Warnings and Precautions (5.6)].

Labor or Delivery: Opioid-dependent women on methadone maintenance therapy may require additional analgesia during labor.

Monitor neonates exposed to opioid analgesics during labor for signs of excess sedation and respiratory depression.

Data

Human Data

The majority of available data from clinical trials, observational studies, case series, and case reports on methadone use in pregnancy do not indicate an increased risk of major malformations specifically due to methadone. Findings regarding specific major malformations, decreased fetal growth, premature birth and Sudden Infant Death Syndrome have been inconsistent. Children prenatally exposed to methadone have been reported to demonstrate mild but persistent deficits in performance on psychometric and behavioral tests and visual abnormalities.

In a multicenter, double-blind, randomized, controlled trial [Maternal Opioid Treatment: Human Experimental Research (MOTHER)] designed primarily to assess neonatal opioid withdrawal effects, opioid-dependent pregnant women were randomized to buprenorphine (n=86) or methadone (n=89) treatment, with enrollment at an average gestational age of 18.7 weeks in both groups. A total of 28 of the 86 women in the buprenorphine group (33%) and 16 of the 89 women in the methadone group (18%) discontinued treatment before the end of pregnancy.

Among women who remained in treatment until delivery, there was no difference between methadone-treated and buprenorphine-treated groups in the number of neonates requiring NOWS treatment or in the peak severity of NOWS. Buprenorphine-exposed neonates required less morphine (mean total dose, 1.1 mg vs. 10.4 mg), had shorter hospital stays (10.0 days vs. 17.5 days), and shorter duration of treatment for NOWS (4.1 days vs. 9.9 days) compared to the methadone-exposed group. There were no differences between groups in other primary outcomes (neonatal head circumference), or secondary outcomes (weight and length at birth, preterm birth, gestational age at delivery, and 1-minute and 5-minute Apgar scores), or in the rates of maternal or neonatal adverse events. The outcomes among mothers who discontinued treatment before delivery and may have relapsed to illicit opioid use are not known. Because of the imbalance in discontinuation rates between the methadone and buprenorphine groups, the study findings are difficult to interpret.

Animal Data

Formal reproductive and developmental toxicology studies for methadone have not been conducted. Exposure margins for the following published study reports are based on a human daily dose (HDD) of 120 mg methadone using a body surface area comparison.

In a published study in pregnant hamsters, a single subcutaneous dose of methadone ranging from 31 mg/kg (2 times the HDD) to 185 mg/kg on Gestation Day 8 resulted in a decrease in the number of fetuses per litter and an increase in the percentage of fetuses exhibiting neural tube defects including exencephaly, cranioschisis, and “various other lesions.” The majority of the doses tested also resulted in maternal death. In a study in pregnant JBT/Jd mice, a single subcutaneous dose of 22 to 24 mg/kg methadone (approximately equivalent to the HDD) administered on Gestation Day 9 produced exencephaly in 11% of the embryos. In another study in pregnant mice, subcutaneous doses up to 28 mg/kg/day methadone (equivalent to the HDD) administered from Gestation Day 6 to 15 resulted in no malformations, but there were increased post-implantation loss and decreased live fetuses at 10 mg/kg/day or greater (0.4 times the HDD) and decreased ossification and fetal body weight at 20 mg/kg/day or greater (0.8 times the HDD). In a second study of pregnant mice dosed with subcutaneous doses up to 28 mg/kg/day methadone from Gestation Day 6 to 15, there was decreased pup viability, delayed onset of development of negative phototaxis and eye opening, increased righting reflexes at 5 mg/kg/day or greater (0.2 times the HDD), and decreased number of live pups at birth and decreased pup weight gain at 20 mg/kg/day or greater (0.8 times the HDD).

No effects were reported in a study of pregnant rats and rabbits at oral doses up to 40 mg/kg (3 and 6 times, respectively, the HDD) administered from Gestation Days 6 to 15 and 6 to 18, respectively.

When pregnant rats were treated with intraperitoneal doses of 2.5, 5, or 7.5 mg/kg methadone from one week prior to mating, through gestation until the end of lactation period, 5 mg/kg or greater (0.4 times the HDD) methadone resulted in decreases in litter size and live pups born and 7.5 mg/kg (0.6 times the HDD) resulted in decreased birth weights. Furthermore, decreased pup viability and pup body weight gain at 2.5 mg/kg or greater (0.2 times the HDD) were noted during the preweaning period.

Additional animal data demonstrate evidence for neurochemical changes in the brains of offspring from methadone-treated pregnant rats, including changes to the cholinergic, dopaminergic, noradrenergic and serotonergic systems at doses below the HDD. Other animal studies have reported that prenatal and/or postnatal exposure to opioids including methadone alters neuronal development and behavior in the offspring including alterations in learning ability, motor activity, thermal regulation, nociceptive responses, and sensitivity to drugs at doses below the HDD. Treatment of pregnant rats subcutaneously with 5 mg/kg methadone from Gestation Day 14 to 19 (0.4 times the HDD) reduced fetal blood testosterone and androstenedione in males.

Published animal data have reported increased neonatal mortality in the offspring of male rodents that were treated with methadone at doses comparable to and less than the HDD for 1 to 12 days before and/or during mating (with more pronounced effects in the first 4 days). In these studies, the female rodents were not treated with methadone, indicating paternally-mediated developmental toxicity. Specifically, methadone administered to the male rat prior to mating with methadone-naïve females resulted in decreased weight gain in progeny after weaning. The male progeny demonstrated reduced thymus weights, whereas the female progeny demonstrated increased adrenal weights. Behavioral testing of these male and female progeny revealed significant differences in behavioral tests compared to control animals, suggesting that paternal methadone exposure can produce physiological and behavioral changes in progeny in this model. Examination of uterine contents of methadone-naïve female mice bred to methadone-treated male mice (once a day for three consecutive days) indicated that methadone treatment produced an increase in the rate of preimplantation deaths in all post-meiotic states at 1 mg/kg/day or greater (0.04 times the HDD). Chromosome analysis revealed a dose-dependent increase in the frequency of chromosomal abnormalities at 1 mg/kg/day or greater.

Studies demonstrated that methadone treatment of male rats for 21 to 32 days prior to mating with methadone-naïve females did not produce any adverse effects, suggesting that prolonged methadone treatment of the male rat resulted in tolerance to the developmental toxicities noted in the progeny. Mechanistic studies in this rat model suggest that the developmental effects of “paternal” methadone on the progeny appear to be due to decreased testosterone production. These animal data mirror the reported clinical findings of decreased testosterone levels in human males on methadone maintenance therapy for opioid addiction and in males receiving chronic intraspinal opioids.

8.2 Lactation

Risk Summary

Based on two small clinical studies, methadone was present in low levels in human milk, but the exposed infants in these studies did not show adverse reactions. Based on an average milk consumption of 150 mL/kg/day, an infant would consume approximately 17.4 mcg/kg/day which is approximately 2 to 3% of the oral maternal dose. There have been rare case reports of sedation and respiratory depression in infants exposed to methadone through breast milk (see Data). Monitor infants exposed to DISKETS through breastmilk for excess sedation and respiratory depression. The developmental and health benefits of breastfeeding should be considered along with the mother’s clinical need for methadone and any potential adverse effects on the breastfed child from the drug or from the underlying maternal condition.

Data

In a study of ten breastfeeding women maintained on oral methadone doses of 10 to 80 mg/day, methadone concentrations from 50 to 570 mcg/L in milk were reported, which, in the majority of samples, were lower than maternal serum drug concentrations at steady state. Peak methadone levels in milk occur approximately 4 to 5 hours after an oral dose.

In a study of twelve breastfeeding women maintained on oral methadone doses of 20 to 80 mg/day, methadone concentrations from 39 to 232 mcg/L in milk were reported. Based on an average milk consumption of 150 mL/kg/day, an infant would consume approximately 17.4 mcg/kg/day, which is approximately 2 to 3% of the oral maternal dose. Methadone has been detected in very low plasma concentrations in some infants whose mothers were taking methadone.

8.3 Females and Males of Reproductive Potential

Infertility

The effect of DISKETS on fertility is unknown. Use of opioids for an extended period of time may cause reduced fertility in females and males of reproductive potential. It is not known whether these effects on fertility are reversible [see Adverse Reactions (6), Clinical Pharmacology (12.2), Nonclinical Pharmacology (13.1)]. Reproductive function in human males may be decreased by methadone treatment. Reductions in ejaculate volume and seminal vesicle and prostate secretions have been reported in methadone-treated individuals. In addition, reductions in serum testosterone levels and sperm motility, and abnormalities in sperm morphology have been reported.

In published animal studies, methadone produces a significant regression of sex accessory organs and testes of male mice and rats and administration of methadone to pregnant rats reduced fetal blood testosterone and androstenedione in male offspring [see Nonclinical Toxicology (13)].

8.4 Pediatric Use

The safety, effectiveness, and pharmacokinetics of methadone in pediatric patients below the age of 18 years have not been established.

8.5 Geriatric Use

Clinical studies of methadone did not include sufficient numbers of subjects aged 65 and over to determine whether they respond differently compared to younger subjects. Other reported clinical experience has not identified differences in responses between elderly and younger patients. In general, start elderly at the low end of the dosing range, taking into account the greater frequency of decreased hepatic, renal, or cardiac function and of concomitant disease or other drug therapy in geriatric patients. Closely monitor elderly patients for signs of respiratory and central nervous system depression.

Methadone is known to be substantially excreted by the kidney, and the risk of adverse reactions to this drug may be greater in patients with impaired renal function. Because elderly patients are more likely to have decreased renal function, care should be taken in dose selection, and it may be useful to monitor renal function.

8.6 Hepatic Impairment

Methadone pharmacokinetics have not been extensively evaluated in patients with hepatic insufficiency. Methadone is metabolized by hepatic pathways; therefore, patients with liver impairment may be at risk of increased systemic exposure to methadone after multiple dosing. Start these patients on lower doses and titrate slowly while carefully monitoring for signs of respiratory and central nervous system depression.

8.7 Renal Impairment

Methadone pharmacokinetics have not been extensively evaluated in patients with renal insufficiency. Since unmetabolized methadone and its metabolites are excreted in urine to a variable degree, start these patients on lower doses and with longer dosing intervals and titrate slowly while carefully monitoring for signs of respiratory and central nervous system depression.

9 DRUG ABUSE AND DEPENDENCE

9.1 Controlled Substance

DISKETS contain methadone, a Schedule II controlled substance.

9.2 Abuse

DISKETS contain methadone, a substance with a high potential for abuse similar to other opioids including fentanyl, hydrocodone, hydromorphone, morphine, oxycodone, oxymorphone, and tapentadol. DISKETS can be abused and is subject to misuse, addiction, and criminal diversion [see Warnings and Precautions (5.5)].

Prescription drug abuse is the intentional non-therapeutic use of a prescription drug, even once, for its rewarding psychological or physiological effects.

Drug addiction is a cluster of behavioral, cognitive, and physiological phenomena that develop after repeated substance use and includes: a strong desire to take the drug, difficulties in controlling its use, persisting in its use despite harmful consequences, a higher priority given to drug use than to other activities and obligations, increased tolerance, and sometimes a physical withdrawal.

“Drug-seeking” behavior is very common in persons with substance use disorders. Drug-seeking tactics include emergency calls or visits near the end of office hours, refusal to undergo appropriate examination, testing or referral, repeated “loss” of prescriptions, tampering with prescriptions, and reluctance to provide prior medical records or contact information for other treating healthcare provider(s). “Doctor shopping” (visiting multiple prescribers to obtain additional prescriptions) is common among drug abusers and people suffering from untreated addiction. Abuse and addiction are separate and distinct from physical dependence and tolerance. Healthcare providers should be aware that addiction may not be accompanied by concurrent tolerance and symptoms of physical dependence in all addicts. In addition, abuse of opioids can occur in the absence of true addiction.

DISKETS, like other opioids, can be diverted for non-medical use into illicit channels of distribution. Careful record-keeping of prescribing information, including quantity and frequency as required by state and federal law, is strongly advised.

Proper assessment and selection of the patient, proper prescribing practices, periodic re-evaluation of therapy, and proper dispensing and storage are appropriate measures that help to limit abuse of opioid drugs.

Risks Specific to DISKETS:

Abuse of methadone poses a risk of overdose and death. This risk is increased with concurrent abuse of methadone with alcohol and other substances. DISKETS are intended for oral use only and must not be injected. Parenteral drug abuse is commonly associated with transmission of infectious diseases such as hepatitis and HIV.

DISKETS Dispersible Tablets, when used for the treatment of opioid addiction in detoxification or maintenance programs, may be dispensed only by opioid treatment programs certified by the Substance Abuse and Mental Health Services Administration (and agencies, practitioners, and institutions by formal agreements with the program sponsor).

9.3 Dependence

Both tolerance and physical dependence can develop during chronic opioid therapy. Tolerance is the need for increasing doses of opioids to maintain a defined effect (in the absence of disease progression or other external factors). Tolerance may occur to both the desired and undesired effects of drugs and may develop at different rates for different effects.

Physical dependence results in withdrawal symptoms after abrupt discontinuation or significant dose reduction of a drug. Withdrawal is also precipitated through the administration of drugs with opioid antagonist activity (e.g., naloxone, nalmefene) or mixed agonist/antagonist analgesics (e.g., pentazocine, butorphanol, nalbuphine), or partial agonists (e.g., buprenorphine). Physical dependence may not occur to a clinically significant degree until after several days to weeks of continued opioid usage. Physical dependence is expected during opioid agonist therapy of opioid addiction.

DISKETS Dispersible Tablets should not be rapidly reduced or abruptly discontinued [see Dosage and Administration (2.6, 2.7)]. If DISKETS Dispersible Tablets are rapidly reduced or abruptly discontinued in a physically dependent patient, a withdrawal syndrome may occur. Some or all of the following can characterize this syndrome: restlessness, lacrimation, rhinorrhea, yawning, perspiration, chills, myalgia, and mydriasis. Other symptoms also may develop, including irritability, anxiety, backache, joint pain, weakness, abdominal cramps, insomnia, nausea, anorexia, vomiting, diarrhea, or increased blood pressure, respiratory rate, or heart rate.

Neonatal opioid withdrawal syndrome (NOWS) is an expected and treatable outcome of prolonged use of opioids during pregnancy [see Warnings and Precautions (5.6)].

10 OVERDOSAGE

Clinical Presentation:

Acute overdosage with methadone can be manifested by respiratory depression, somnolence progressing to stupor or coma, skeletal muscle flaccidity, cold and clammy skin, constricted pupils, and, in some cases, pulmonary edema, bradycardia, hypotension, hypoglycemia, partial or complete airway obstruction, atypical snoring, and death. Marked mydriasis rather than miosis may be seen with hypoxia in overdose situations [see Clinical Pharmacology (12.2)]. In severe overdosage, particularly by the intravenous route, apnea, circulatory collapse, cardiac arrest, and death may occur.

Methadone overdosage is associated with rhabdomyolysis. Seek medical attention, especially if abuse/misuse results in prolonged immobilization. Toxic leukoencephalopathy has been reported after opioid overdose, and can present hours, days, or weeks after apparent recovery from the initial intoxication. Hearing loss has been reported after methadone overdose, in some cases permanent.

Treatment of Overdose:

In case of overdose, priorities are the re-establishment of a patent and protected airway and institution of assisted or controlled ventilation if needed. Employ other supportive measures (including oxygen, vasopressors) in the management of circulatory shock and pulmonary edema as indicated. Cardiac arrest or arrhythmias will require advanced life support techniques.

For clinically significant respiratory or circulatory depression secondary to opioid overdose, administer an opioid overdose reversal agent such as naloxone or nalmefene.

Because the duration of reversal would be expected to be less than the duration of action of methadone, carefully monitor the patient until spontaneous respiration is reliably reestablished. If the response to opioid overdose reversal agent is suboptimal or not sustained, administer additional reversal agent as directed in the product’s prescribing information.

In an individual physically dependent on opioids, administration of the recommended usual dosage of the opioid overdose reversal agent will precipitate an acute withdrawal syndrome. The severity of the withdrawal symptoms experienced will depend on the degree of physical dependence and the dose of the reversal agent administered. If a decision is made to treat serious respiratory depression in the physically dependent patient, administration of the reversal agent should be initiated with care and by titration with smaller than usual doses of the reversal agent.

11 DESCRIPTION

DISKETS Dispersible Tablets (Methadone Hydrochloride Tablets for Oral Suspension USP), contain methadone, an opioid agonist, available as 40 mg dispersible tablets for oral administration. Methadone hydrochloride is chemically described as 6-(dimethylamino)-4,4-diphenyl-3-heptanone hydrochloride. Methadone hydrochloride USP is a fine white powder. It is very soluble in water, soluble in isopropanol and in chloroform, and practically insoluble in ether and in glycerine. It is present in DISKETS Dispersible Tablets as the racemic mixture. Methadone hydrochloride has a melting point of 235°C, a pKa of 8.25 in water at 20°C, a solution (1 part per 100) pH between 4.5 and 6.5, a partition coefficient of 117 at pH 7.4 in octanol/water and a molecular weight of 345.91. Its molecular formula is C21H27NO•HCl and its structural formula is:

Each DISKETS Dispersible Tablet contains 40 mg of methadone hydrochloride USP and the following inactive ingredients: colloidal silicon dioxide, magnesium stearate, microcrystalline cellulose 101, orange lake blend, orange/pineapple flavor, potassium phosphate monobasic, pregelatinized starch and stearic acid.

DISKETS Dispersible Tablets are cross-scored, allowing for flexible dosage adjustment. Each tablet may be broken or cut in half to yield two 20 mg doses, or in quarters to yield four 10 mg doses.

DISKETS Dispersible Tablets (Methadone Hydrochloride Tablets for Oral Suspension USP), are for oral administration following dispersion in a liquid.

DISKETS Dispersible Tablets contain insoluble excipients and must not be injected.

12 CLINICAL PHARMACOLOGY

12.1 Mechanism of Action

Methadone hydrochloride is a mu-agonist; a synthetic opioid with multiple actions qualitatively similar to those of morphine, the most prominent of which involves the central nervous system and organs composed of smooth muscle. The methadone withdrawal syndrome, although qualitatively similar to that of morphine, differs in that the onset is slower, the course is more prolonged, and the symptoms are less severe.

Some data also indicate that methadone acts as an antagonist at the N-methyl-D-aspartate (NMDA) receptor. The contribution of NMDA receptor antagonism to methadone’s efficacy is unknown.

12.2 Pharmacodynamics

Effects on the Central Nervous System:

Methadone produces respiratory depression by direct action on brain stem respiratory centers. The respiratory depression involves a reduction in the responsiveness of the brain stem respiratory centers to both increases in carbon dioxide tension and electrical stimulation.

Methadone causes miosis, even in total darkness. Pinpoint pupils are a sign of opioid overdose but are not pathognomonic (e.g., pontine lesions of hemorrhagic or ischemic origins may produce similar findings). Marked mydriasis rather than miosis may be seen due to hypoxia in overdose situations.

Some NMDA receptor antagonists have been shown to produce neurotoxic effects in animals.

Effects on the Gastrointestinal Tract and Other Smooth Muscle:

Methadone causes a reduction in motility associated with an increase in smooth muscle tone in the antrum of the stomach and duodenum. Digestion of food in the small intestine is delayed and propulsive contractions are decreased. Propulsive peristaltic waves in the colon are decreased, while tone is increased to the point of spasm, resulting in constipation. Other opioid-induced effects may include a reduction in biliary and pancreatic secretions, spasm of sphincter of Oddi, transient elevations in serum amylase, and opioid-induced esophageal dysfunction (OIED).

Effects on the Cardiovascular System:

Methadone produces peripheral vasodilation, which may result in orthostatic hypotension or syncope. Manifestations of histamine release and/or peripheral vasodilation may include pruritus, flushing, red eyes, sweating, and/or orthostatic hypotension.

Effects on the Endocrine System:

Opioids inhibit the secretion of adrenocorticotropic hormone (ACTH), cortisol, and luteinizing hormone (LH) in humans [see Adverse Reactions (6)]. They also stimulate prolactin, growth hormone (GH) secretion, and pancreatic secretion of insulin and glucagon.

Chronic use of opioids may influence the hypothalamic-pituitary-gonadal axis, leading to androgen deficiency that may manifest as low libido, impotence, erectile dysfunction, amenorrhea, or infertility. The causal role of opioids in the clinical syndrome of hypogonadism is unknown because the various medical, physical, lifestyle, and psychological stressors that may influence gonadal hormone levels have not been adequately controlled for in studies conducted to date [see Adverse Reactions (6)].

Effects on the Immune System:

Opioids have been shown to have a variety of effects on components of the immune system in in vitro and animal models. The clinical significance of these findings is unknown. Overall, the effects of opioids appear to be modestly immunosuppressive.

Concentration–Adverse Reaction Relationships:

There is a relationship between increasing methadone plasma concentration and increasing frequency of dose-related opioid adverse reactions such as nausea, vomiting, CNS effects, and respiratory depression. In opioid-tolerant patients, the situation may be altered by the development of tolerance to opioid-related adverse reactions [see Dosage and Administration (2.5, 2.6, 2.7)].

12.3 Pharmacokinetics

Absorption:

Following oral administration the bioavailability of methadone ranges between 36 to 100% and peak plasma concentrations are achieved between 1 to 7.5 hours. Dose proportionality of methadone pharmacokinetics is not known. However, after administration of daily oral doses ranging from 10 to 225 mg, the steady-state plasma concentrations ranged between 65 to 630 ng/mL and the peak concentrations ranged between 124 to 1,255 ng/mL. Effect of food on the bioavailability of methadone has not been evaluated.

Distribution:

Methadone is a lipophilic drug and the steady-state volume of distribution ranges between 1 to 8 L/kg. In plasma, methadone is predominantly bound to α1-acid glycoprotein (85% to 90%). Methadone is secreted in saliva, breast milk, amniotic fluid and umbilical cord plasma.

Elimination:

Metabolism: Methadone is primarily metabolized by N-demethylation to an inactive metabolite, 2-ethylidene-1,5-dimethyl-3,3-diphenylpyrrolidene(EDDP). Cytochrome P450 enzymes, primarily CYP3A4, CYP2B6, CYP2C19, CYP2C9 and CYP2D6, are responsible for conversion of methadone to EDDP and other inactive metabolites, which are excreted mainly in the urine. Methadone appears to be a substrate for P-glycoprotein but its pharmacokinetics do not appear to be significantly altered in case of P-glycoprotein polymorphism or inhibition.

Excretion: The elimination of methadone is mediated by extensive biotransformation, followed by renal and fecal excretion. Published reports indicate that after multiple dose administration the apparent plasma clearance of methadone ranged between 1.4 and 126 L/h, and the terminal half-life (T1/2) was highly variable and ranged between 8 to 59 hours in different studies. Methadone is a basic (pKa=9.2) compound and the pH of the urinary tract can alter its disposition in plasma. Also, since methadone is lipophilic, it has been known to persist in the liver and other tissues. The slow release from the liver and other tissues may prolong the duration of methadone action despite low plasma concentrations.

Drug Interaction Studies:

Cytochrome P450 Interactions: Methadone undergoes hepatic N-demethylation by cytochrome P450 (CYP) isoforms, principally CYP3A4, CYP2B6, CYP2C19, CYP2C9, and CYP2D6. Co-administration of methadone with CYP inducers may result in more rapid metabolism and potential for decreased effects of methadone, whereas administration with CYP inhibitors may reduce metabolism and potentiate methadone’s effects. Although antiretroviral drugs such as efavirenz, nelfinavir, nevirapine, ritonavir, lopinavir+ritonavir combination are known to inhibit some CYPs, they are shown to reduce the plasma levels of methadone, possibly due to CYP induction activity [see Drug Interactions (7)].

Cytochrome P450 Inducers: The following drug interactions were reported following co-administration of methadone with known inducers of cytochrome P450 enzymes:

Rifampin: In patients well-stabilized on methadone, concomitant administration of rifampin resulted in a marked reduction in serum methadone levels and a concurrent appearance of withdrawal symptoms.
Phenytoin:In a pharmacokinetic study with patients on methadone maintenance therapy, phenytoin administration (250 mg twice daily initially for 1 day followed by 300 mg daily for 3 to 4 days) resulted in an approximately 50% reduction in methadone exposure and withdrawal symptoms occurred concurrently. Upon discontinuation of phenytoin, the incidence of withdrawal symptoms decreased and methadone exposure increased to a level comparable to that prior to phenytoin administration.
St. John’s Wort, Phenobarbital, Carbamazepine:Administration of methadone with other CYP3A4 inducers may result in withdrawal symptoms.

Cytochrome P450 Inhibitors:

Voriconazole: Voriconazole can inhibit the activity of CYP3A4, CYP2C9, and CYP2C19. Repeat dose administration of oral voriconazole (400 mg every 12 hours for 1 day, then 200 mg every 12 hours for 4 days) increased the peak plasma concentration (Cmax) and AUC of (R)-methadone by 31% and 47%, respectively, in subjects receiving a methadone maintenance dose (30 to 100 mg daily). The Cmax and AUC of (S)-methadone increased by 65% and 103%, respectively. Increased plasma concentrations of methadone have been associated with toxicity including QT prolongation. Frequent monitoring for adverse events and toxicity related to methadone is recommended during co-administration. Dose reduction of methadone may be needed [see Drug Interactions (7)].

Antiretroviral Drugs: Although antiretroviral drugs such as efavirenz, nelfinavir, nevirapine, ritonavir, telaprevir, lopinavir+ritonavir combination are known to inhibit some CYPs, they are shown to reduce the plasma levels of methadone, possibly due to CYP induction activity.

Abacavir, amprenavir, darunavir+ritonavir, efavirenz, nelfinavir, nevirapine, ritonavir, telaprevir, lopinavir+ritonavir, saquinavir+ritonavir, tipranavir+ritonavir combination: Co-administration of these anti-retroviral agents resulted in increased clearance or decreased plasma levels of methadone [see Drug Interactions (7)].
Didanosine and Stavudine:Methadone decreased the AUC and peak levels for didanosine and stavudine, with a more significant decrease for didanosine. Methadone disposition was not substantially altered [see Drug Interactions (7)].
Zidovudine:Methadone increased the AUC of zidovudine which could result in toxic effects [see Drug Interactions (7)].

13 NONCLINICAL TOXICOLOGY

13.1 Carcinogenesis, Mutagenesis, Impairment of Fertility

Carcinogenesis:

The results of carcinogenicity assessment in B6C2F1 mice and Fischer 344 rats following dietary administration of two doses of methadone HCl have been published. Mice consumed 15 mg/kg/day or 60 mg/kg/day methadone for two years. These doses were approximately 0.6 and 2.5 times a human daily oral dose of 120 mg/day on a body surface area basis (HDD). There was a significant increase in pituitary adenomas in female mice treated with 15 mg/kg/day but not with 60 mg/kg/day. Under the conditions of the assay, there was no clear evidence for a treatment-related increase in the incidence of neoplasms in male rats. Due to decreased food consumption in males at the high dose, male rats consumed 16 mg/kg/day and 28 mg/kg/day of methadone for two years. These doses were approximately 1.3 and 2.3 times the HDD. In contrast, female rats consumed 46 mg/kg/day or 88 mg/kg/day for two years. These doses were approximately 3.7 and 7.1 times the HDD. Under the conditions of the assay, there was no clear evidence for a treatment-related increase in the incidence of neoplasms in either male or female rats.

Mutagenesis:

There are several published reports on the potential genetic toxicity of methadone. Methadone tested positive in the in vivo mouse dominant lethal assay and the in vivo mammalian spermatogonial chromosome aberration test. Additionally, methadone tested positive in the E. coli DNA repair system and Neurospora crassa and mouse lymphoma forward mutation assays. In contrast, methadone tested negative in tests for chromosome breakage and disjunction and sex-linked recessive lethal gene mutations in germ cells of Drosophila using feeding and injection procedures.

Fertility:

Published animal studies show that methadone treatment of males can alter reproductive function. Methadone produces decreased sexual activity (mating) of male rats at 10 mg/kg/day (corresponding to 0.3 times the human daily oral dose of 120 mg/day based on body surface area). Methadone also produces a significant regression of sex accessory organs and testes of male mice and rats at 0.2 and 0.8 times the HDD, respectively. Methadone treatment of pregnant rats from Gestation Day 14 to 19 reduced fetal blood testosterone and androstenedione in males. Decreased serum levels of testosterone were observed in male rats that were treated with methadone (1.3 to 3.3 mg/kg/day for 14 days, corresponding to 0.1 to 0.3 times the HDD) or 10 to 15 mg/kg/day for 10 days (0.8 to 1.2 times the HDD).

16 HOW SUPPLIED/STORAGE AND HANDLING

DISKETS Dispersible Tablets (Methadone Hydrochloride Tablets for Oral Suspension USP)

40 mg supplied as light pinkish orange, pillow shaped, compressed dispersible tablet with product identification “54 883” debossed on one side and cross scored on the other side.

NDC 0054-4538-25: Bottle of 100 Dispersible Tablets

DISKETS Dispersible Tablets, if dispensed, must be packaged in child-resistant containers.

Store at 25°C (77°F); excursions permitted to 15° to 30°C (59° to 86°F) [see USP Controlled Room Temperature].

Store DISKETS Dispersible Tablets securely and dispose of properly [see Patient Counseling Information (17)].

17 PATIENT COUNSELING INFORMATION

Provide the following information to patients receiving DISKETS Dispersible Tablets or to their caregivers:

Life-Threatening Respiratory Depression:

Discuss the risk of respiratory depression with patients, explaining that the risk is greatest when starting DISKETS Dispersible Tablets or when the dose is increased.

Educate patients and caregivers on how to recognize respiratory depression and emphasize the importance of calling 911 or getting emergency medical help right away in the event of a known or suspected overdose [see Warnings and Precautions (5.1)].

Patient Access to an Opioid Overdose Reversal Agent for the Emergency Treatment of Opioid Overdose:

Inform patients and caregivers about opioid overdose reversal agents (e.g., naloxone, nalmefene) and discuss the importance of having access to an opioid overdose reversal agent. Because patients being treated with methadone may be at risk for opioid overdose during initiation or titration, or in the case of relapse to illicit use, discuss the importance of having access to an opioid overdose reversal agent. Also discuss the importance of having access to an opioid overdose reversal agent if the patient has household members (including children) or other close contacts at risk for accidental ingestion or opioid overdose.

Discuss with the patient the options for obtaining an opioid overdose reversal agent (e.g., prescription, over-the-counter (some products), or as part of a community-based program) [see Dosage and Administration (2.3), Warnings and Precautions (5.1)].

There are important differences among the opioid overdose reversal agents. Be familiar with these differences, as outlined in the approved labeling for those products, prior to recommending or prescribing such an agent.

Educate patients and caregivers on how to recognize the signs and symptoms of an opioid overdose.

Explain to patients and caregivers that effects of opioid overdose reversal agents like naloxone and nalmefene are temporary, and that they must call 911 or get emergency medical help right away in all cases of known or suspected opioid overdose, even if an opioid overdose reversal agent is administered. Repeat administration may be necessary, particularly for overdose involving DISKETS Dispersible Tablets [see Dosage and Administration (2.3), Warnings and Precautions (5.1), Overdosage (10)].

Advise patients and caregivers:

- how to treat with an opioid overdose reversal agent in the event of an opioid overdose.
- to tell family and friends about their opioid overdose reversal agent, and to keep it in a place where family and friends can easily access it in an emergency.
- to read the Patient Information (or other educational material) that will come with their opioid overdose reversal agent. Emphasize the importance of doing this before an opioid emergency happens, so the patient and caregiver will know what to do.

Interactions with Benzodiazepines and Other CNS Depressants:

Inform patients and caregivers that potentially fatal additive effects may occur if DISKETS Dispersible Tablets are used with benzodiazepines or other CNS depressants (e.g., alcohol, non-benzodiazepine sedative/hypnotics, anxiolytics, tranquilizers, muscle relaxants, general anesthetics, antipsychotics, gabapentinoids [gabapentin or pregabalin], and other opioids) and not to use these concomitantly unless supervised by a healthcare provider [see Warnings and Precautions (5.2)].

Symptoms of Arrhythmia:

Instruct patients to seek medical attention immediately if they experience symptoms suggestive of an arrhythmia (such as palpitations, near syncope, or syncope) when taking DISKETS Dispersible Tablets [see Warnings and Precautions (5.3)].

Accidental Ingestion:

Inform patients that accidental ingestion, especially by children, may result in respiratory depression or death [see Warnings and Precautions (5.4)]. Instruct patients to take steps to store DISKETS Dispersible Tablets securely. Advise patients to dispose of unused DISKETS Dispersible Tablets by flushing the tablets down the toilet.

Abuse Potential:

Inform patients that DISKETS Dispersible Tablets contain methadone, a Schedule II controlled substance that is subject to abuse [see Warnings and Precautions (5.5)]. Instruct patients not to share DISKETS Dispersible Tablets with others and to take steps to protect DISKETS Dispersible Tablets from theft or misuse.

Important Administration Instructions [see Dosage and Administration (2)]:

Instruct patients how to properly take DISKETS Dispersible Tablets, including the following:

- DISKETS Dispersible Tablets are for oral administration only and must be initially dispersed in liquid before use. After dispersion in liquid, the preparation must not be injected.
- Inform patients that DISKETS Dispersible Tablets should be taken only as directed to reduce the risk of life-threatening adverse reactions (e.g., respiratory depression), and the dose should not be adjusted without consulting a physician or other healthcare professional.
- Reassure patients initiating treatment with DISKETS Dispersible Tablets for opioid dependence that the dose of methadone will “hold” for longer periods of time as treatment progresses.
- Apprise patients seeking to discontinue treatment with methadone for opioid dependence of the high risk of relapse to illicit drug use associated with discontinuation of DISKETS Dispersible Tablets maintenance treatment.
- Advise patients not to discontinue DISKETS Dispersible Tablets without first discussing the need for a tapering regimen with the prescriber.

Serotonin Syndrome:

Inform patients that DISKETS could cause a rare but potentially life-threatening condition resulting from concomitant administration of serotonergic drugs. Warn patients of the symptoms of serotonin syndrome and to seek medical attention right away if symptoms develop. Instruct patients to inform their physicians if they are taking, or plan to take serotonergic medications [see Warnings and Precautions (5.9), Drug Interactions (7)].

MAOI Interaction:

Inform patients to avoid taking DISKETS while using any drugs that inhibit monoamine oxidase. Patients should not start MAOIs while taking DISKETS [see Drug Interactions (7)].

Adrenal Insufficiency:

Inform patients that DISKETS could cause adrenal insufficiency, a potentially life-threatening condition. Adrenal insufficiency may present with non-specific symptoms and signs such as nausea, vomiting, anorexia, fatigue, weakness, dizziness, and low blood pressure. Advise patients to seek medical attention if they experience a constellation of these symptoms [see Warnings and Precautions (5.10)].

Hypotension:

Inform patients that DISKETS Dispersible Tablets may cause orthostatic hypotension and syncope. Instruct patients on how to recognize symptoms of low blood pressure and how to reduce the risk of serious consequences should hypotension occur (e.g., sit or lie down, carefully rise from a sitting or lying position) [see Warnings and Precautions (5.11)].

Anaphylaxis:

Inform patients that anaphylaxis has been reported with ingredients contained in DISKETS Dispersible Tablets. Advise patients how to recognize such a reaction and when to seek medical attention [see Adverse Reactions (6)].

Neonatal Opioid Withdrawal:

Advise women that if they are pregnant while being treated with DISKETS, the baby may have signs of withdrawal at birth and that withdrawal is treatable [see Warnings and Precautions (5.6), Specific Populations (8.1)].

Lactation:

Advise women who are breastfeeding to monitor the infant for increased sleepiness (more than usual), difficulty breathing or limpness. Instruct nursing mothers using DISKETS Dispersible Tablets to watch for signs of methadone toxicity in their infants, which include increased sleepiness (more than usual), difficulty breastfeeding, breathing difficulties, or limpness. Instruct nursing mothers to talk to their baby’s healthcare provider immediately if they notice these signs. If they cannot reach the healthcare provider right away, instruct them to take the baby to the emergency room or call 911 (or local emergency services) [see Use in Specific Populations (8.2)].

Infertility:

Advise patients that use of opioids, such as DISKETS Dispersible Tablets, for an extended period of time may cause reduced fertility. It is not known whether these effects on fertility are reversible [see Use in Specific Populations (8.3)].

Driving or Operating Heavy Machinery:

Inform patients that DISKETS Dispersible Tablets may impair the ability to perform potentially hazardous activities such as driving or operating heavy machinery. Advise patients not to perform such tasks until they know how they will react to the medication [see Warnings and Precautions (5.16)].

Constipation:

Advise patients of the potential for severe constipation, including management instructions and when to seek medical attention [see Adverse Reactions (6), Clinical Pharmacology (12.2)].

Hypoglycemia:

Inform patients that methadone may cause hypoglycemia. Instruct patients how to recognize that symptoms of low blood glucose and to contact their healthcare provider if these symptoms occur [see Warnings and Precautions (5.17)].

Distributed by:

Hikma Pharmaceuticals USA Inc.

Berkeley Heights, NJ 07922

C50000737/04

Package/Label Display Panel

NDC 0054-4538-25

Rx only